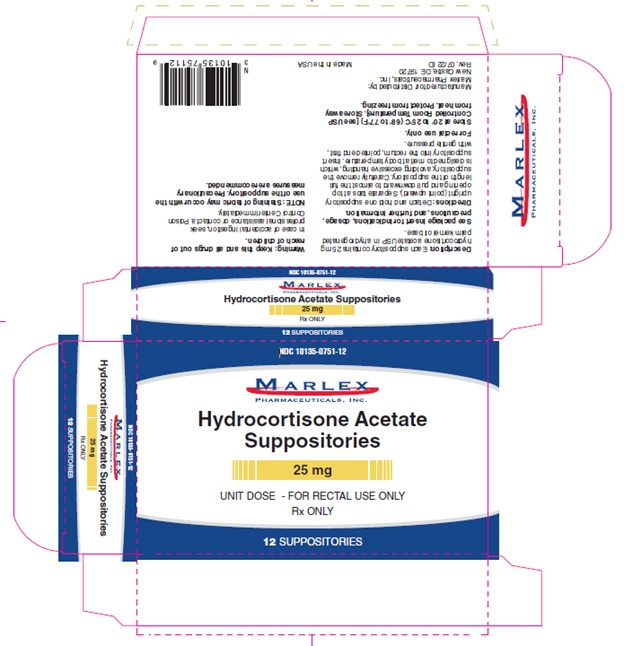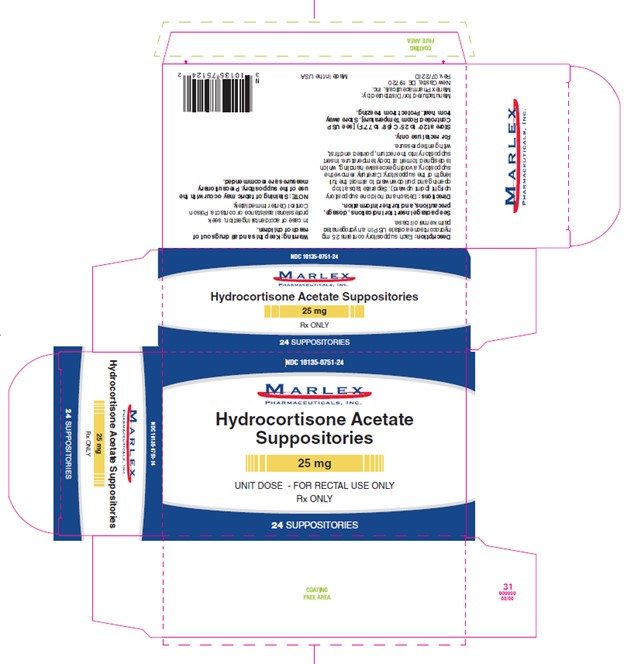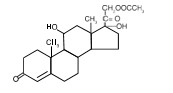 DRUG LABEL: Hydrocortisone Acetate
NDC: 10135-751 | Form: SUPPOSITORY
Manufacturer: Marlex Pharmaceuticals, Inc.
Category: prescription | Type: HUMAN PRESCRIPTION DRUG LABEL
Date: 20251113

ACTIVE INGREDIENTS: HYDROCORTISONE ACETATE 25 mg/1 1
INACTIVE INGREDIENTS: HYDROGENATED PALM OIL

Hydrocortisone Acetate Suppositories
Rx Only

DESCRIPTION

Each Hydrocortisone Acetate Suppository for rectal administration contains hydrocortisone acetate USP in a hydrogenated palm kernel oil base.

Hydrocortisone acetate is a corticosteroid. The molecular weight of hydrocortisone acetate is 404.50. Chemically, hydrocortisone acetate is pregn-4-ene-3, 20 dione, 21- (acetyloxy)-11, 17-dihydroxy-, (11β)- with an empirical formula of C23 H32O6 and the following structural formula:

CLINICAL PHARMACOLOGY

In normal subjects, about 26 percent of hydrocortisone acetate is absorbed when the hydrocortisone acetate suppository is applied to the rectum. Absorption of hydrocortisone acetate may vary across abraded or inflamed surfaces.

Topical steroids are primarily effective because of their anti-inflammatory, antipruritic and vasoconstrictive action.

INDICATIONS AND USAGE

Hydrocortisone Acetate Suppositories are indicated for use in inflamed hemorrhoids, post irradiation (factitial) proctitis, as an adjunct in the treatment of chronic ulcerative colitis, cryptitis, other inflammatory conditions of the anorectum, and pruritus ani.

CONTRAINDICATIONS

Hydrocortisone Acetate Suppositories are contraindicated in those patients with a history of hypersensitivity to any of the components.

PRECAUTIONS

Do not use unless adequate proctologic examination is made.

If irritation develops, the product should be discontinued, and appropriate therapy instituted.

In the presence of an infection, the use of an appropriate antifungal or antibacterial agent should be instituted. If a favorable response does not occur promptly, Hydrocortisone Acetate Suppositories should be discontinued until the infection has been adequately controlled.

Carcinogenesis

No long-term studies in animals have been performed to evaluate the carcinogenic potential of corticosteroid suppositories.

PREGNANCY CATEGORY C

In laboratory animals, topical steroids have been associated with an increase in the incidence of fetal abnormalities when gestating females have been exposed to rather low dosage levels. There are no adequate and well-controlled studies in pregnant women.

Hydrocortisone acetate suppositories should only be used during pregnancy if the potential benefit justifies the risk to the fetus. Drugs of this class should not be used extensively on pregnant patients, in large amounts, or for prolonged periods of time.

It is not known whether this drug is excreted in human milk. Because many drugs are excreted in human milk and because of the potential for serious adverse reactions in nursing infants from hydrocortisone acetate suppositories, a decision should be made whether to discontinue nursing or to discontinue the drug, taking into account the importance of the drug to the mother.

ADVERSE REACTIONS

The following local adverse reactions have been reported with Hydrocortisone Acetate Suppositories: burning, itching, irritation, dryness, folliculitis, hypopigmentation, allergic contact dermatitis, and secondary infection.

To report SUSPECTED ADVERSE REACTIONS, contact Marlex Pharmaceuticals at 1-888-582-1953 or drugsafety@marlexpharm.com or FDA at 1-800-FDA-1088 or www.fda.gov/medwatch.

Drug abuse and dependence have not been reported in patients treated with Hydrocortisone Acetate Suppositories.

DOSAGE AND ADMINISTRATION

For rectal administration: Insert one suppository in the rectum twice daily, morning and night for two weeks, in nonspecific proctitis.ln more severe cases, one suppository three times a day or two suppositories twice daily. In factitial proctitis, the recommended duration of therapy is six to eight weeks or less, according to the response of the individual case.

Detach and hold one suppository upright(point upward). Separate tabs at top opening and pull downward to almost the full length of the suppository. Carefully remove the suppository, avoiding excessive handling, which is designed to melt at body temperature. Insert suppository into the rectum, pointed end first, with gentle pressure.

HOW SUPPLIED

25mg (12 count) NDC 10135-0751-12

25mg (24 count) NDC 10135-0751-24

Store at 20° to 25°C (68° to 77°F) [see USP Controlled Room Temperature]. Store away from heat. Protect from freezing.

Manufactured for/ Distributed by:

Marlex Pharmaceuticals, Inc.

New Castle, DE 19720

Rev. 07/22 ID

PRINCIPAL DISPLAY PANEL - 25 mg Suppository Carton

NDC 10135-0751-12

Rx Only

Hydrocortisone Acetate
Suppositories

25 mg

FOR RECTAL USE ONLY

12 Suppositories

PRINCIPAL DISPLAY PANEL - 25 mg Suppository Carton

NDC 10135-0751-24

Rx Only

Hydrocortisone Acetate
Suppositories

25 mg

FOR RECTAL USE ONLY

24 Suppositories